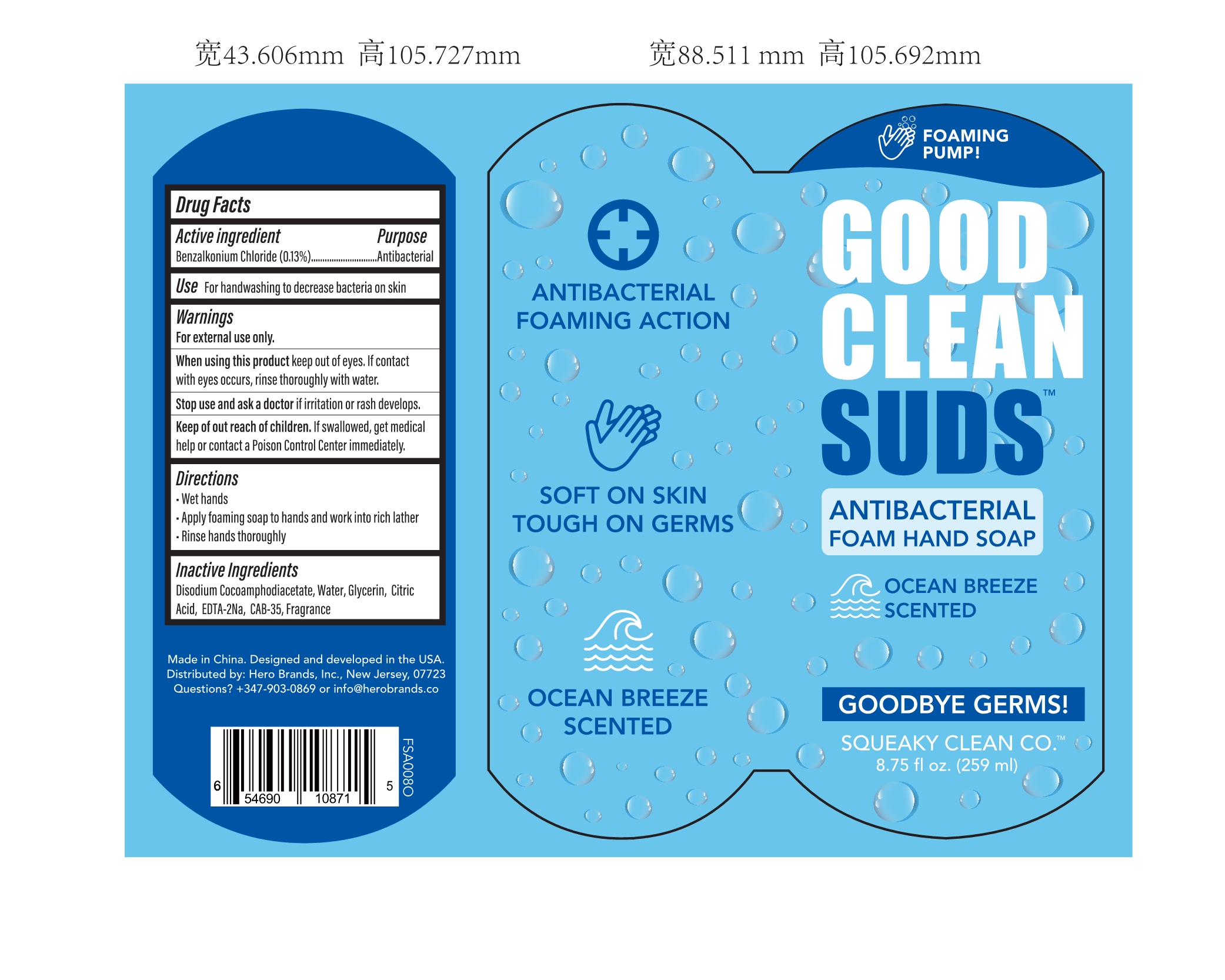 DRUG LABEL: 8.75oz ANTIBACTERIAL FOAM HANDSOAP - OCEAN BREEZE
NDC: 90114-253 | Form: GEL
Manufacturer: Hero Brands, Inc.
Category: otc | Type: HUMAN OTC DRUG LABEL
Date: 20201205

ACTIVE INGREDIENTS: BENZALKONIUM CHLORIDE 0.013 g/100 mL
INACTIVE INGREDIENTS: SHEA BUTTER; EDETIC ACID; WATER; COCAMIDOPROPYL BETAINE; CITRIC ACID MONOHYDRATE; GLYCERIN; DISODIUM COCOAMPHODIACETATE

90114-253 259 ml Zorin Pharmaceutical Technology (Hangzhou) Co Ltd. 8.75oz ANTIBACTERIAL FOAM HAND SOAP - OCEAN BREEZE

Active Ingredient(s)

Benzalkonium Chloride 0.13% , Antibacterial

Purpose

Antibacterial, Hand SOAP

Use

For handwashing to decrease bacteria on skin.

Warnings

For external use only. Keep away from fire or flame

Do not use

- in children less than 2 months of age
- on open skin wounds

When using this product keep out of eyes. If contact with eyes occurs, rinse thoroughly with water.

Stop use and ask a doctor if irritation or rash develops.

Keep out of reach of children. If swallowed, get medical help or contact a Poison Control Center immediately.

Directions

- Wet hands
- Apply foaming soap to hands and work into rich lather
- Rinse hands thoroughly

Inactive ingredients

Disodium Cocoamphodiacetate,Water,Glycerin,Citric Acid, EDTA-2Na,CAB-35,Fragrance